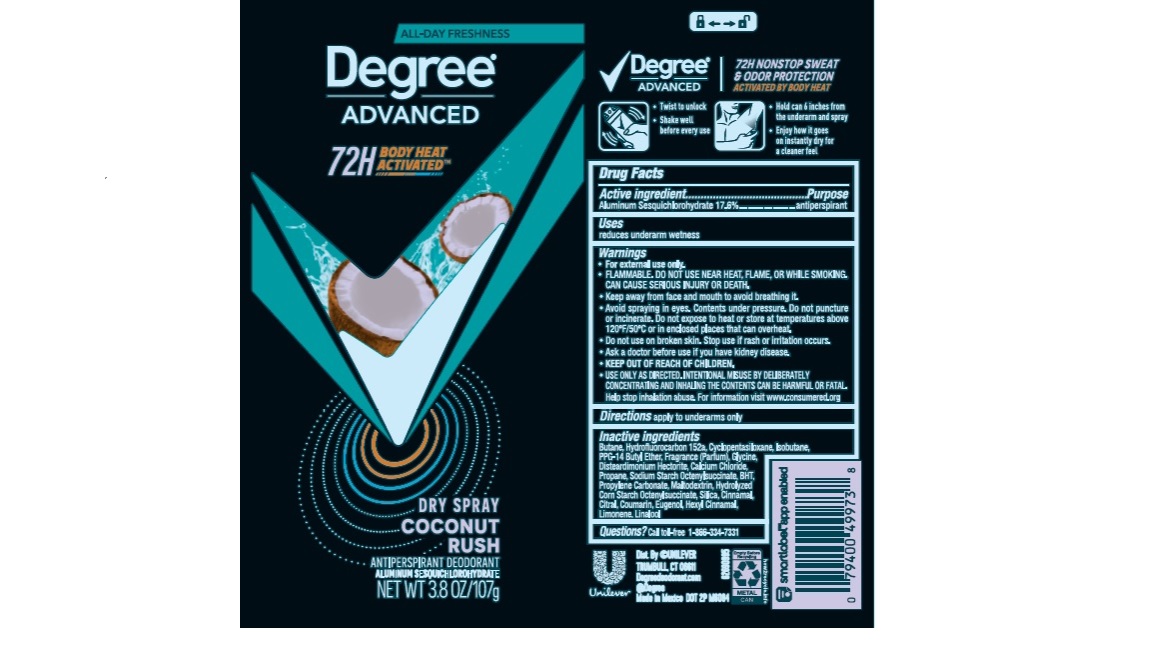 DRUG LABEL: Degree
NDC: 64942-2202 | Form: AEROSOL, SPRAY
Manufacturer: Conopco, Inc. d/b/a Unilever
Category: otc | Type: HUMAN OTC DRUG LABEL
Date: 20241106

ACTIVE INGREDIENTS: ALUMINUM SESQUICHLOROHYDRATE 17.6 g/100 g
INACTIVE INGREDIENTS: MALTODEXTRIN; PROPYLENE CARBONATE; SILICON DIOXIDE; GLYCINE; LIMONENE, (+)-; ISOBUTANE; .BETA.-CITRONELLOL, (R)-; BUTANE; 1,1-DIFLUOROETHANE; CYCLOMETHICONE 5; PPG-14 BUTYL ETHER; DISTEARDIMONIUM HECTORITE; CALCIUM CHLORIDE; .ALPHA.-HEXYLCINNAMALDEHYDE; LINALOOL, (+/-)-; PROPANE; BUTYLATED HYDROXYTOLUENE; GERANIOL; ISOMETHYL-.ALPHA.-IONONE; BENZYL ALCOHOL; BENZYL SALICYLATE; COUMARIN

Degree Advanced Coconut Rush Dry Spray 72H Antiperspirant Deodorant

Drug Facts

Active ingredient

Aluminum Sesquichlorohydrate (17.6%)

Purpose

antiperspirant

Uses

reduces underarm wetness

Directions

For underarms use only

Inactive ingredients

Butane, Hydrofluorocarbon 152a, Cyclopentasiloxane, Isobutane, PPG-14 Butyl Ether, Fragrance (Parfum), Glycine, Disteardimonium Hectorite, Calcium Chloride, Propane, Sodium Starch Octenylsuccinate, BHT, Propylene Carbonate, Maltodextrin, Hydrolyzed Corn Starch Octenylsuccinate, Silica, Alpha-Isomethyl Ionone, Benzyl Alcohol, Benzyl Salicylate, Citronellol, Coumarin, Geraniol, Hexyl Cinnamal, Limonene, Linalool

Questions?

Call toll-free 1-866-334-7331